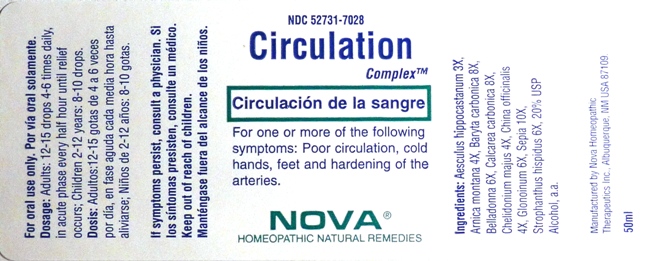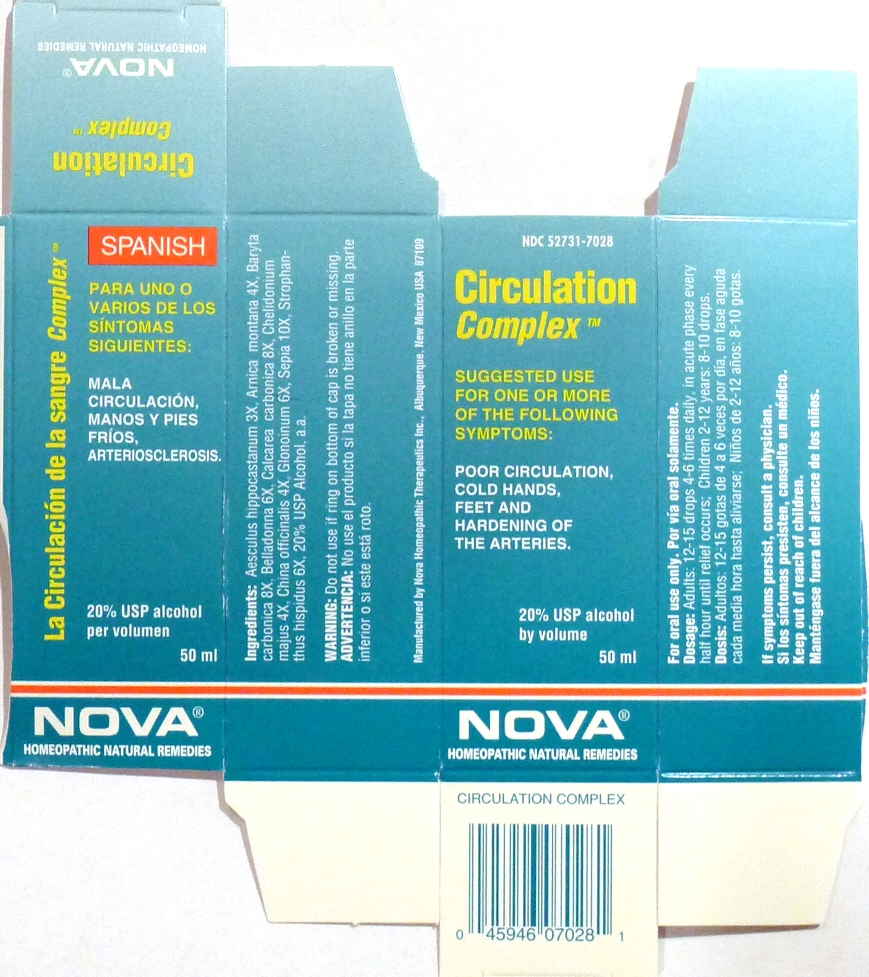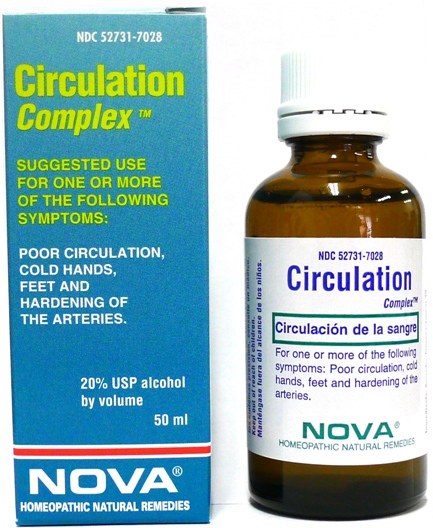 DRUG LABEL: Circulation Complex
NDC: 52731-7028 | Form: LIQUID
Manufacturer: Nova Homeopathic Therapeutics, Inc.
Category: homeopathic | Type: HUMAN OTC DRUG LABEL
Date: 20110601

ACTIVE INGREDIENTS: HORSE CHESTNUT 3 [hp_X]/1 mL; ARNICA MONTANA 4 [hp_X]/1 mL; BARIUM CARBONATE 8 [hp_X]/1 mL; ATROPA BELLADONNA 6 [hp_X]/1 mL; OYSTER SHELL CALCIUM CARBONATE, CRUDE 8 [hp_X]/1 mL; CHELIDONIUM MAJUS 4 [hp_X]/1 mL; CINCHONA PUBESCENS BARK 4 [hp_X]/1 mL; NITROGLYCERIN 6 [hp_X]/1 mL; SEPIA OFFICINALIS JUICE 10 [hp_X]/1 mL; STROPHANTHUS HISPIDUS SEED 6 [hp_X]/1 mL
INACTIVE INGREDIENTS: ALCOHOL

Circulation Complex

Purpose:

Suggested use for one or more of the following symptoms:

Poor circulation, cold hands, feet and hardening of the arteries.

Usage and Dosage:

For oral use only.

DOSAGE AND ADMINISTRATION

Adults:
In Acute Phase:
12-15 drops, every half hour until relief occurs
When Relief Occurs:
12-15 drops, 4-6 times per day
Children 2-12 years:
8-10 drops, 4-6 times per day

Warnings:

Keep out of reach of children.

WARNINGS

If symptoms persist, consult a physician.
Do not use if ring on bottom of cap is broken or missing.

Active Ingredients:

Aesculus hippocastanum 3X, Arnica montana 4X, Baryta carbonica 8X, Belladonna 6X, Calcarea carbonica 8X, Chelidonium majus 4X, China officinalis 4X, Glonoinum 6X, Sepia 10X, Strophanthus hispidus 6X

Inactive Ingredients:

Alcohol, 20% USP

QUESTIONS

Manufactured by Nova Homeopathic Therapeutics Inc., Albuquerque, New Mexico USA 87109
1-800-225-8094

PACKAGE LABEL

Circulation Complex Product

Circulation Complex Bottle Label

Circulation Complex Box